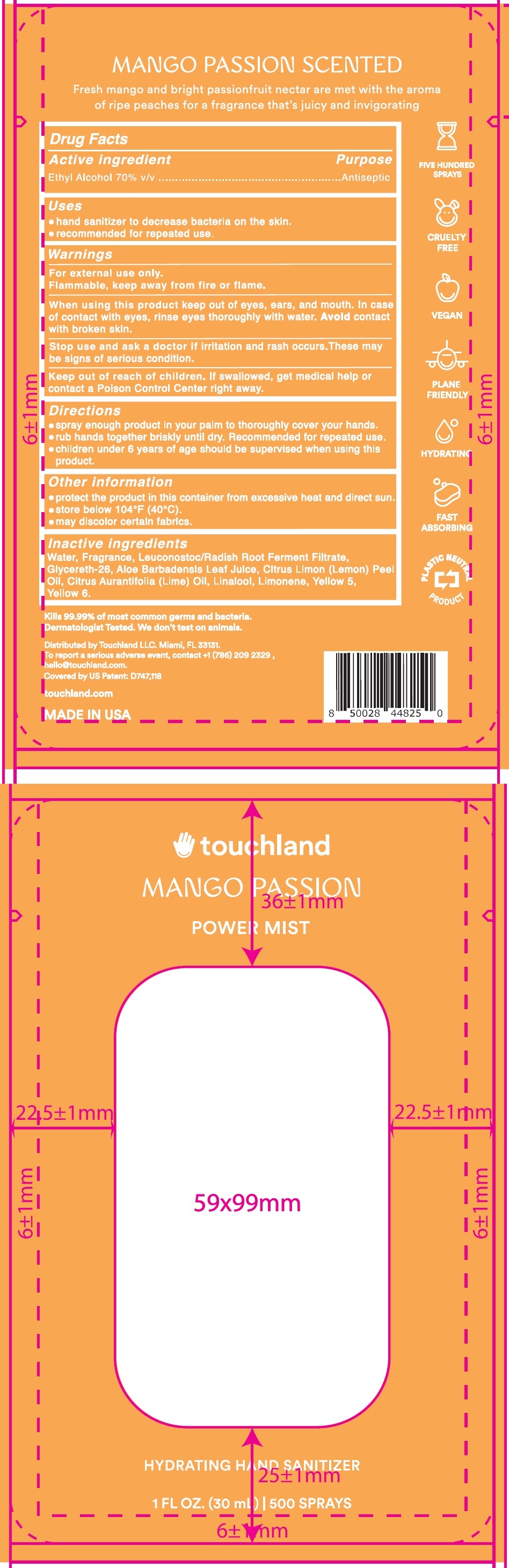 DRUG LABEL: Touchland Power Mist Hydrating Hand Sanitizer Mango Passion
NDC: 72033-216 | Form: SPRAY
Manufacturer: TOUCHLAND LLC
Category: otc | Type: HUMAN OTC DRUG LABEL
Date: 20231228

ACTIVE INGREDIENTS: ALCOHOL 70 mL/100 mL
INACTIVE INGREDIENTS: WATER; LEUCONOSTOC/RADISH ROOT FERMENT FILTRATE; GLYCERETH-26; ALOE VERA LEAF; LEMON OIL, COLD PRESSED; LIME OIL, COLD PRESSED; LINALOOL, (+/-)-; LIMONENE, (+/-)-; FD&C YELLOW NO. 5; FD&C YELLOW NO. 6

Touchland Power Mist Hydrating Hand Sanitizer Mango Passion

Active ingredients

Ethyl Alcohol 70% v/v

Purpose

Antiseptic

Uses

- hand sanitizer to decrease bacteria on the skin.
- recommended for repeted use.

Warnings

For external use only. Flammable , keep away from fire or flame.

When using this product

keep out of eyes, ears, and mouth. In case of contact with eyes, rinse eyes thoroughly with water. Aviod contact with broken skin.

Stop use and ask a doctor

if irritation and rash occurs. These may be signs of serious condition.

Keep out of reach of children.

If swallowed, get medical help or contact a poison Control Center right away.

Directions

- spray enough product in your plam to thoroughly cover your hands.
- rub hands together briskly until dry. Recommended for repeted use.
- children under 6 years of age should be supervised when using this product.

Other information

- rotect the product in this container from excessive heat and direct sun.
- store below 104°F(40°C).
- may dlscolor certain fabrics.

Inactive ingredients

Water, Fragrance, Leuconostoc/Radish Root Ferment Filtrate, Glycereth-26, Aloe Barbadensis Leaf Julce, Cltrus Lemon (Lemon) Peel Oil, Citrus Aurantifolia (Lime) Oil, Linanool, Limonene, Yellow 5, Yellow 6.